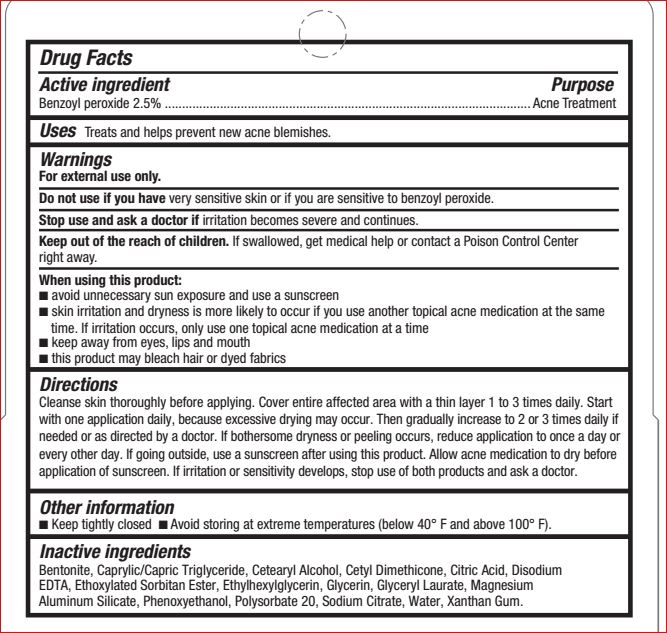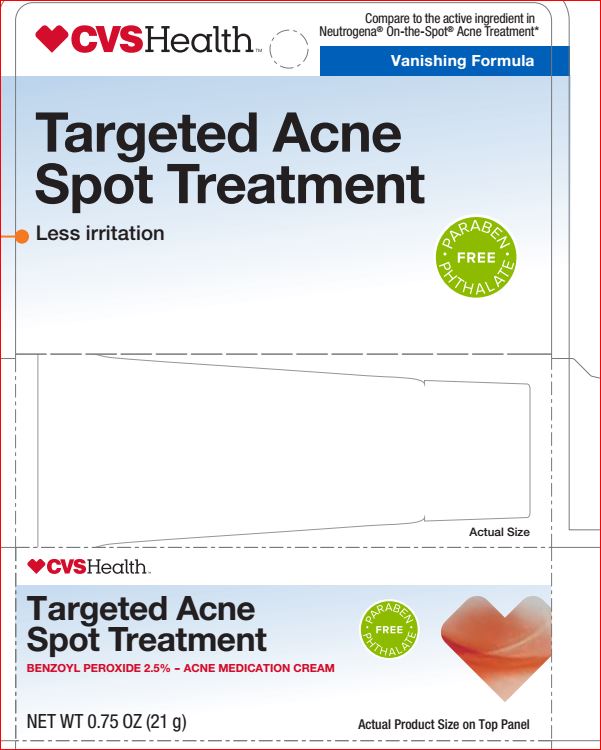 DRUG LABEL: Targeted Acne Spot Treatment
NDC: 69842-888 | Form: LOTION
Manufacturer: CVS
Category: otc | Type: HUMAN OTC DRUG LABEL
Date: 20180509

ACTIVE INGREDIENTS: Benzoyl Peroxide 2.5 g/100 g
INACTIVE INGREDIENTS: Bentonite; MEDIUM-CHAIN TRIGLYCERIDES; ANHYDROUS CITRIC ACID; EDETATE DISODIUM ANHYDROUS; Ethylhexylglycerin; Glycerin; Glyceryl Laurate; Magnesium Aluminum Silicate; Phenoxyethanol; Polysorbate 20; Sodium Citrate; Water; Xanthan Gum

CVS Health
Drug Facts

Active ingredient Purpose
Benzoyl peroxide 2.5% ................ ................. Acne Treatment

INDICATIONS AND USAGE

Uses Helps prevent new acne blemishes.

Warnings
For external use only.
Do not use if you have very sensitive skin or if you are sensitive to benzoyl peroxide.
Stop use and ask a doctor if irritation becomes severe.
When using this product:
■ avoid unnecessary sun exposure and use a sunscreen
■ using other topical acne drugs at the same time or right after use may increase dryness or irritation of skin.
If this occurs, only one drug should be used
■ skin irritation may occur, characterized by redness, burning, itching, peeling, or possibly swelling. Irritation
may be reduced by using the product less frequently or in a lower concentration
■ keep away from eyes, lips and mouth
■ avoid contact with hair and dyed fabrics, which may be bleached by this product

KEEP OUT OF REACH OF CHILDREN

Keep out of the reach of children. If swallowed, get medical help or contact a Poison Control Center
right away.

Directions
Cleanse skin thoroughly before applying. Cover entire affected area with a thin layer 1 to 3 times daily. Start
with one application daily, because excessive drying may occur. Then gradually increase to 2 or 3 times daily
if needed or as directed by a doctor. If bothersome dryness or peeling occurs, reduce application to once a
day or every other day. If going outside use a sunscreen. Allow acne medication to dry before application of
sunscreen. If irritation or sensitivity develops, stop use of both products and ask a doctor.

Inactive ingredients
Bentonite, Caprylic/Capric Triglyceride, Cetyl Dimethicone, Citric Acid, Disodium EDTA, Emulsifying Wax NF,
Ethylhexylglycerin, Glycerin, Glyceryl Laurate, Magnesium Aluminum Silicate, Phenoxyethanol, Polysorbate 20,
Sodium Citrate, Water, Xanthan Gum.